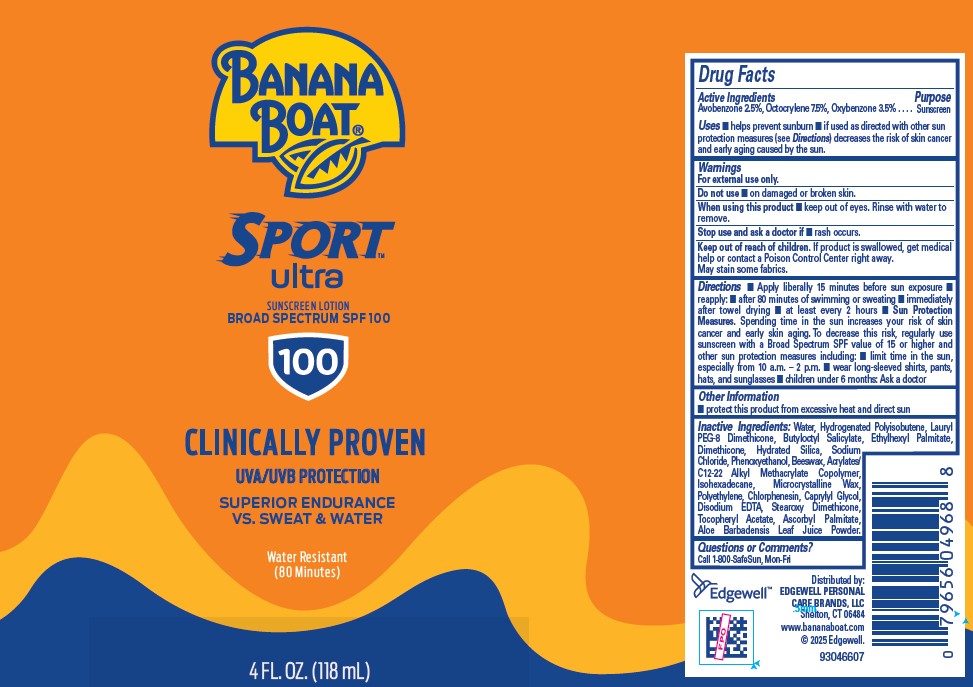 DRUG LABEL: BANANA BOAT
NDC: 63354-381 | Form: LOTION
Manufacturer: Edgewell Personal Care Brands LLC
Category: otc | Type: HUMAN OTC DRUG LABEL
Date: 20250813

ACTIVE INGREDIENTS: AVOBENZONE 2.5 g/100 g; OCTOCRYLENE 7.5 g/100 g; OXYBENZONE 3.5 g/100 g
INACTIVE INGREDIENTS: LAURYL PEG-8 DIMETHICONE (300 CPS); HYDROGENATED POLYISOBUTENE 8; HYDRATED SILICA; POLYETHYLENE; CHLORPHENESIN; PHENOXYETHANOL; DIMETHICONE; EDETATE DISODIUM; ISOHEXADECANE; ETHYLHEXYL PALMITATE; MICROCRYSTALLINE WAX; ALOE BARBADENSIS LEAF POWDER; WATER; SODIUM CHLORIDE; ASCORBYL PALMITATE; BUTYLOCTYL SALICYLATE; BEESWAX; CAPRYLYL GLYCOL; .ALPHA.-TOCOPHEROL ACETATE

Active Ingredient

Avobenzone 2.5%, Octocrylene 7.5%, Oxybenzone 3.5% .

Purpose

Sunscreen

Uses

■ helps prevent sunburn ■ if used as directed with other sun protection measures (see Directions), decreases the risk of skin cancer and early skin aging caused by the sun.

Warnings

For external use only.

May stain some fabrics.

Do not use

■ on damaged or broken skin.

When using this product

■ keep out of eyes. Rinse with water to remove.

Stop use and ask a doctor if

■ rash occurs.

Keep out of reach of children.

If product is swallowed, get medical help or contact a Poison Control Center right away.

Directions

■ apply liberally 15 minutes before sun exposure ■ reapply: ■ after 80 minutes of swimming or sweating ■ immediately after towel drying ■ at least every 2 hours ■ Sun Protection Measures. Spending time in the sun increases your risk of skin cancer and early skin aging. To decrease this risk, regularly use a sunscreen with a broad spectrum SPF value of 15 or higher and other sun protection measures including: ■ limit time in the sun, especially from 10 a.m. – 2 p.m. ■ wear long-sleeved shirts, pants, hats, and sunglasses ■ children under 6 months: Ask a doctor

Other information

■ protect the product in this container from excessive heat and direct sun

Inactive ingredients

Water, Hydrogenated Polyisobutene, Lauryl PEG-8 Dimethicone, Butyloctyl Salicylate, Ethylhexyl Palmitate, Dimethicone, Hydrated Silica, Sodium Chloride, Phenoxyethanol, Beeswax, Acrylates/ C12-22 Alkyl Methacrylate Copolymer, Isohexadecane, Microcrystalline Wax, Polyethylene, Chlorphenesin, Caprylyl Glycol, Disodium EDTA, Stearoxy Dimethicone, Tocopheryl Acetate, Ascorbyl Palmitate, Aloe Barbadensis Leaf Juice Powder.

Questions or Comments?

Call 1-800-SafeSun, Mon-Fri

PRINCIPAL DISPLAY PANEL

BANANA
BOAT
SPORT
ULTRA
SUNSCREEN LOTION
BROAD SPECTRUM SPF 100
100
CLINICALLY PROVEN
UVA/UVB PROTECTION
SUPERIOR ENDURANCE
VS. SWEAT & WATER
WATER RESISTANT
(80 Minutes)
4 FL. OZ. (118 mL)